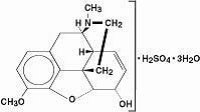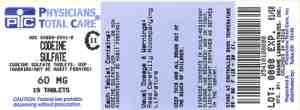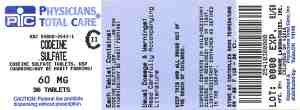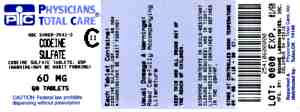 DRUG LABEL: Codeine Sulfate
NDC: 54868-2541 | Form: TABLET
Manufacturer: Physicians Total Care, Inc.
Category: prescription | Type: HUMAN PRESCRIPTION DRUG LABEL
Date: 20091022
DEA Schedule: CII

ACTIVE INGREDIENTS: CODEINE SULFATE 60 mg/1 1
INACTIVE INGREDIENTS: SILICON DIOXIDE; CELLULOSE, MICROCRYSTALLINE; STARCH, CORN; STEARIC ACID

1 INDICATIONS AND USAGE

Codeine sulfate is an opioid analgesic indicated for the relief of mild to moderately severe pain where the use of an opioid analgesic is appropriate.

2 DOSAGE AND ADMINISTRATION

Selection of patients for treatment with codeine sulfate should be governed by the same principles that apply to the use of similar opioid analgesics. Physicians should individualize treatment in every case, using non-opioid analgesics, opioids on an as needed basis and/or combination products, and chronic opioid therapy in a progressive plan of pain management.

2.1 Individualization of Dosage

As with any opioid drug product, adjust the dosing regimen for each patient individually, taking into account the patient’s prior analgesic treatment experience. In the selection of the initial dose of codeine sulfate, attention should be given to the following:

• the total daily dose, potency and specific characteristics of the opioid the patient has been taking previously;

• the reliability of the relative potency estimate used to calculate the equivalent codeine sulfate dose needed;

• the patient’s degree of opioid tolerance;

• the general condition and medical status of the patient;

• concurrent medications;

• the type and severity of the patient’s pain;

• risk factors for abuse, addiction or diversion, including a prior history of abuse, addiction or diversion.

The following dosing recommendations, therefore, can only be considered suggested approaches to what is actually a series of clinical decisions over time in the management of the pain of each individual patient.

Continual re-evaluation of the patient receiving codeine sulfate is important, with special attention to the maintenance of pain control and the relative incidence of side effects associated with therapy. During chronic therapy, especially for noncancer-related pain, the continued need for the use of opioid analgesics should be re-assessed as appropriate.

During periods of changing analgesic requirements, including initial titration, frequent contact is recommended between physician, other members of the healthcare team, the patient, and the caregiver/family.

2.2 Initiation of Therapy

The usual adult dosage for tablets is 15 mg to 60 mg repeated up to every four hours as needed for pain. The maximum 24 hour dose is 360 mg.

The initial dose should be titrated based upon the individual patient’s response to their initial dose of codeine. This dose can then be adjusted to an acceptable level of analgesia taking into account the improvement in pain intensity and the tolerability of the codeine by the patient.

It should be kept in mind, however, that tolerance to codeine sulfate can develop with continued use and that the incidence of untoward effects is dose-related. Adult doses of codeine higher than 60 mg fail to give commensurate relief of pain and are associated with an appreciably increased incidence of undesirable side effects.

2.3 Cessation of Therapy

When the patient no longer requires therapy with codeine sulfate, doses should be tapered gradually to prevent signs and symptoms of withdrawal in the physically dependent patient.

3 DOSAGE FORMS AND STRENGTHS

Each 15 mg tablet for oral administration contains 15 mg of codeine sulfate. It is a white, biconvex tablet scored on one side, with strength-indicating number “15” debossed on the scored side and product identification number “54 613” debossed on the other side.

Each 30 mg tablet for oral administration contains 30 mg of codeine sulfate. It is a white, biconvex tablet scored on one side, with strength-indicating number “30” debossed on the scored side and product identification number “54 783” debossed on the other side.

Each 60 mg tablet for oral administration contains 60 mg of codeine sulfate. It is a white, biconvex tablet scored on one side, with strength-indicating number “60” debossed on the scored side and product identification number “54 412” debossed on the other side.

4 CONTRAINDICATIONS

Codeine sulfate is contraindicated in patients with known hypersensitivity to codeine or any components of the product. Persons known to be hypersensitive to certain other opioids may exhibit cross-sensitivity to codeine.

Codeine sulfate is contraindicated in patients with respiratory depression in the absence of resuscitative equipment.

Codeine sulfate is contraindicated in patients with acute or severe bronchial asthma or hypercarbia.

Codeine sulfate is contraindicated in any patient who has or is suspected of having paralytic ileus.

5 WARNINGS AND PRECAUTIONS

5.1 Respiratory Depression

Respiratory depression is the primary risk of codeine sulfate. Respiratory depression occurs more frequently in elderly or debilitated patients and in those suffering from conditions accompanied by hypoxia, hypercapnia, or upper airway obstruction, in whom even moderate therapeutic doses may significantly decrease pulmonary ventilation. Codeine produces dose-related respiratory depression.

Caution should be exercised when codeine sulfate is used postoperatively, in patients with pulmonary disease or shortness of breath, or whenever ventilatory function is depressed. Opioid related respiratory depression occurs more frequently in elderly or debilitated patients and in those suffering from conditions accompanied by hypoxia, hypercapnia, or upper airway obstruction, in whom even moderate therapeutic doses may significantly decrease pulmonary ventilation. Opioids, including codeine sulfate, should be used with extreme caution in patients with chronic obstructive pulmonary disease or cor pulmonale and in patients having a substantially decreased respiratory reserve (e.g., severe kyphoscoliosis), hypoxia, hypercapnia, or pre-existing respiratory depression. In such patients, even usual therapeutic doses of codeine sulfate may increase airway resistance and decrease respiratory drive to the point of apnea. Alternative non-opioid analgesics should be considered, and codeine sulfate should be employed only under careful medical supervision at the lowest effective dose in such patients. [see 10 OVERDOSAGE]

5.2 Misuse and Abuse of Opioids

Codeine sulfate is an opioid agonist of the morphine-type and a Schedule II controlled substance. Such drugs are sought by drug abusers and people with addiction disorders. Diversion of Schedule II products is an act subject to criminal penalty.

Codeine can be abused in a manner similar to other opioid agonists, legal or illicit. This should be considered when prescribing or dispensing codeine sulfate in situations where the physician or pharmacist is concerned about an increased risk of misuse, abuse, or diversion.

Misuse and abuse of codeine sulfate poses a significant risk to the abuser that could result in overdose and death. Codeine may be abused by crushing, chewing, snorting or injecting the product. [see 9 DRUG ABUSE AND DEPENDENCE]

Concerns about abuse and addiction should not prevent the proper management of pain. Healthcare professionals should contact their State Professional Licensing Board or State Controlled Substances Authority for information on how to prevent and detect abuse or diversion of this product.

5.3 Interaction with Alcohol and Drugs of Abuse

Codeine sulfate may be expected to have additive effects when used in conjunction with alcohol, other opioids, or illicit drugs that cause central nervous system depression, because respiratory depression, hypotension, profound sedation, coma or death may result.

5.4 Head Injury and Increased Intracranial Pressure

Respiratory depressant effects of opioids and their capacity to elevate cerebrospinal fluid pressure resulting from vasodilation following CO2 retention may be markedly exaggerated in the presence of head injury, other intracranial lesions or a pre-existing increase in intracranial pressure. Furthermore, opioids including codeine sulfate, produce adverse reactions which may obscure the clinical course of patients with head injuries.

5.5 Hypotensive Effect

Codeine sulfate may cause severe hypotension in an individual whose ability to maintain blood pressure has already been compromised by a depleted blood volume or concurrent administration of drugs such as phenothiazines or general anesthetics. Codeine sulfate may produce orthostatic hypotension and syncope in ambulatory patients.

Codeine sulfate should be administered with caution to patients in circulatory shock, as vasodilation produced by the drug may further reduce cardiac output and blood pressure.

5.6 Gastrointestinal Effects

Codeine sulfate should not be administered to patients with gastrointestinal obstruction, especially paralytic ileus because codeine sulfate diminishes propulsive peristaltic waves in the gastrointestinal tract and may prolong the obstruction.

Chronic use of opioids, including codeine sulfate, may result in obstructive bowel disease especially in patients with underlying intestinal motility disorder. Codeine sulfate may cause or aggravate constipation.

Administration of codeine sulfate may obscure the diagnosis or clinical course of patients with acute abdominal conditions.

5.7 Use in Pancreatic/Biliary Tract Disease

Codeine sulfate should be used in caution in patients with biliary tract disease, including acute pancreatitis, as codeine sulfate may cause spasm of the sphincter of Oddi and diminish biliary and pancreatic secretions.

5.8 Special Risk Patients

As with other opioids, codeine sulfate should be used with caution in elderly or debilitated patients and those with severe impairment of hepatic or renal function, hypothyrodism, Addison’s disease, prostatic hypertrophy or urethral stricture. [see 8 USE IN SPECIFIC POPULATIONS] The usual precautions should be observed and the possibility of respiratory depression should be kept in mind.

Caution should be exercised in the administration of codeine sulfate to patients with CNS depression, acute alcoholism, and delirium tremens.

All opioids may aggravate convulsions in patients with convulsive disorders, and all opioids may induce or aggravate seizures in some clinical settings.

5.9 Ultra-Rapid Metabolizers of Codeine

Some individuals may be ultra-rapid metabolizers due to a specific CYP2D6*2x2 genotype. These individuals convert codeine into its active metabolite, morphine, more rapidly and completely than other people. This rapid conversion results in higher than expected serum morphine levels. Even at labeled dosage regimens, individuals who are ultra-rapid metabolizers may experience overdose symptoms such as extreme sleepiness, confusion, or shallow breathing.

The prevalence of this CYP2D6 phenotype varies widely and has been estimated at 0.5 to 1% in Chinese and Japanese, 0.5 to 1% in Hispanics, 1 to 10% in Caucasians, 3% in African Americans, and 16 to 28% in North Africans, Ethiopians, and Arabs. Data are not available for other ethnic groups.

When physicians prescribe codeine-containing drugs, they should choose the lowest effective dose for the shortest period of time and inform their patients about these risks and the signs of morphine overdose. [see 8 USE IN SPECIFIC POPULATIONS]

5.10 Driving and Operating Machinery

Patients should be cautioned that codeine sulfate could impair the mental and/or physical abilities needed to perform potentially hazardous activities such as driving a car or operating machinery.

Patients should also be cautioned about the potential combined effects of codeine sulfate with other CNS depressants, including opioids, phenothiazines, sedative/hypnotics, and alcohol. [see 7 DRUG INTERACTIONS]

6 ADVERSE REACTIONS

Serious adverse reactions associated with codeine are respiratory depression and, to a lesser degree, circulatory depression, respiratory arrest, shock, and cardiac arrest.

The most frequently observed adverse reactions with codeine administration include drowsiness, lightheadedness, dizziness, sedation, shortness of breath, nausea, vomiting, sweating, and constipation.

Other adverse reactions include allergic reactions, euphoria, dysphoria, abdominal pain, and pruritis.

Other less frequently observed adverse reactions expected from opioid analgesics, including codeine sulfate, include:

Cardiovascular system: faintness, flushing, hypotension, palpitations, syncope

Digestive System: abdominal cramps, anorexia, diarrhea, dry mouth, gastrointestinal distress, pancreatitis

Nervous system: anxiety, drowsiness, fatigue, headache, insomnia, nervousness, shakiness, somnolence, vertigo, visual disturbances, weakness

Skin and Appendages: rash, sweating, urticaria

7 DRUG INTERACTIONS

7.1 CNS Depressants

Concurrent use of other opioids, antihistamines, antipsychotics, antianxiety agents, or other CNS depressants (including sedatives, hypnotics, general anesthetics, antiemetics, phenothiazines, or other tranquilizers or alcohol) concomitantly with codeine sulfate tablets may result in additive CNS depression, respiratory depression, hypotension, profound sedation, or coma. Use codeine sulfate with caution and in reduced dosages in patients taking these agents.

7.2 Mixed Agonist/Antagonist Opioid Analgesics

Mixed agonist/antagonist analgesics (i.e., pentazocine, nalbuphine, and butorphanol) should NOT be administered to patients who have received or are receiving a course of therapy with a pure opioid agonist analgesic such as codeine sulfate. In these patients, mixed agonist/antagonist analgesics may reduce the analgesic effect and/or may precipitate withdrawal symptoms.

7.3 Anticholinergics

Anticholinergics or other medications with anticholinergic activity when used concurrently with opioid analgesics including codeine sulfate, may result in increased risk of urinary retention and/or severe constipation, which may lead to paralytic ileus.

7.4 Antidepressants

Use of MAO inhibitors or tricyclic antidepressants with codeine sulfate may increase the effect of either the antidepressant or codeine. MAOIs markedly potentiate the action of morphine sulfate, the major metabolite of codeine. Codeine should not be used in patients taking MAOIs or within 14 days of stopping such treatment.

7.5 Metabolic Enzymes

Patients taking cytochrome P-450 enzyme inducers or inhibitors may demonstrate an altered response to codeine, therefore analgesic activity should be monitored. Codeine sulfate is metabolized by the cytochrome P-450 3A4 and 2D6 isoenzymes. [see 12 CLINICAL PHARMACOLOGY] The concurrent use of drugs that preferentially induce codeine N-demethylation (cytochrome P-450 3A4) may increase the plasma concentrations of codeine’s inactive metabolite norcodeine. Drugs that are strong inhibitors of codeine O-demethylation (cytochrome P-450 2D6) may decrease the plasma concentrations of codeine’s active metabolites, morphine and morphine-6-glucuronide. The contribution of these active metabolites to the overall analgesic effect of codeine is not fully understood, but should be considered.

7.6 Drug-Laboratory Test Interaction

Codeine sulfate tablets may cause an elevation of plasma amylase and lipase due to the potential of codeine to produce spasm of the sphincter of Oddi. Determination of these enzyme levels may be unreliable for some time after an opiate agonist has been given.

8 USE IN SPECIFIC POPULATIONS

Enter section text here

9 DRUG ABUSE AND DEPENDENCE

9.1 Controlled Substance

Codeine sulfate is an opioid agonist and is a Schedule II controlled substance. Codeine sulfate can be abused and is subject to criminal diversion.

9.2 Abuse

Drug addiction is characterized by compulsive use, use for non-medical purposes, and continued use despite harm or risk of harm. Drug addiction is a treatable disease, utilizing a multi-disciplinary approach, but relapse is common.

“Drug seeking” behavior is very common in addicts and drug abusers. Drug-seeking tactics include emergency calls or visits near the end of office hours, refusal to undergo appropriate examination, testing or referral, repeated “loss” of prescriptions, tampering with prescriptions and reluctance to provide prior medical records or contact information for other treating physician(s). “Doctor shopping” to obtain additional prescriptions is common among drug abusers and people suffering from untreated addiction.

Abuse and addiction are separate and distinct from physical dependence and tolerance. Physicians should be aware that addiction may not be accompanied by concurrent tolerance and symptoms of physical dependence. The converse is also true. In addition, abuse of opioids can occur in the absence of true addiction and is characterized by misuse for non-medical purposes, often in combination with other psychoactive substances. Careful record-keeping of prescribing information, including quantity, frequency, and renewal requests is strongly advised.

Codeine is intended for oral use only. Abuse of codeine poses a risk of overdose and death. The risk is increased with concurrent abuse of alcohol and other substances. Parenteral drug abuse is commonly associated with transmission of infectious diseases such as hepatitis and HIV.

Proper assessment of the patient, proper prescribing practices, periodic re-evaluation of therapy, and proper dispensing and storage are appropriate measures that help to limit abuse of opioid drugs.

Infants born to mothers physically dependent on opioids will also be physically dependent and may exhibit respiratory difficulties and withdrawal symptoms. [see 8 USE IN SPECIFIC POPULATIONS]

9.3 Dependence

Tolerance is the need for increasing doses of opioids to maintain a defined effect such as analgesia (in the absence of disease progression or other external factors). Physical dependence is manifested by withdrawal symptoms after abrupt discontinuation of a drug or upon administration of an antagonist. Physical dependence and tolerance are not unusual during chronic opioid therapy.

The opioid abstinence or withdrawal syndrome is characterized by some or all of the following: restlessness, lacrimation, rhinorrhea, yawning, perspiration, chills, myalgia, and mydriasis. Other symptoms also may develop, including irritability, anxiety, backache, joint pain, weakness, abdominal cramps, insomnia, nausea, anorexia, vomiting, diarrhea, or increased blood pressure, respiratory rate, or heart rate.

In general, opioids should not be abruptly discontinued.

10 OVERDOSAGE

10.1 Symptoms

Acute overdose of codeine is characterized by respiratory depression (a decrease in respiratory rate and/or tidal volume, Cheyne-Stokes respiration, cyanosis), extreme somnolence progressing to stupor or coma, miosis (mydriasis may occur in terminal narcosis or severe hypoxia), skeletal muscle flaccidity, cold and clammy skin, and sometimes bradycardia and hypotension. In severe overdosage, apnea, circulatory collapse, cardiac arrest, and death may occur.

Codeine sulfate may cause miosis, even in total darkness. Pinpoint pupils are a sign of opioid overdose but are not pathognomonic (e.g., pontine lesions of hemorrhagic or ischemic origin may produce similar findings). Marked mydriasis rather than miosis may be seen with hypoxia in overdose situations.

10.2 Treatment

Primary attention should be given to the re-establishment of adequate respiratory exchange through provision of a patent airway and institution of assisted or controlled ventilation as necessary. Supportive measures (including oxygen and vasopressors) should be employed in the management of circulatory shock and pulmonary edema accompanying overdose as indicated. Cardiac arrest or arrhythmias may require cardiac massage or defibrillation. Induction of emesis is not recommended because of the potential for CNS depression and seizures. Activated charcoal is recommended if the patient is awake and able to protect his/her airway. In persons who are at risk for abrupt onset of seizures or mental status depression, activated charcoal should be administered by medical or paramedical personnel capable of airway management to prevent aspiration in the event of spontaneous emesis. Severe agitation or seizures should be treated with an intravenous benzodiazepine.

The opioid antagonist naloxone hydrochloride is a specific antidote against respiratory depression resulting from overdosage or unusual sensitivity to opiate agonists, including codeine. Therefore, an appropriate dose of naloxone hydrochloride (see prescribing information for naloxone hydrochloride) should be administered, preferably by the intravenous route, simultaneously with efforts at respiratory resuscitation. Since the duration of action of codeine may exceed that of the antagonist, the patient should be kept under continued surveillance and repeated doses of the antagonist should be administered as needed to maintain adequate respiration. A narcotic antagonist should not be administered in the absence of clinically significant respiratory or cardiovascular depression secondary to codeine sulfate overdose.

In an individual physically dependent on opioids, administration of the usual dose of the antagonist will precipitate an acute withdrawal syndrome. The severity of the withdrawal symptoms experienced will depend on the degree of physical dependence and the dose of the antagonist administered. Use of an opioid antagonist should be reserved for cases where such treatment is clearly needed. If it is necessary to treat serious respiratory depression in the physically dependent patient, administration of the antagonist should be initiated with care and titrated with smaller than usual doses.

11 DESCRIPTION

Chemically, codeine is Morphinan-6-ol,7,8-didehydro-4,5-epoxy-3-methoxy-17-methyl-(5α,6α)-, sulfate (2:1) (salt), trihydrate. Its empirical formula is C18H21NO3 and its molecular weight is 299.36.

Its structure is as follows:

Each tablet contains 15, 30, or 60 mg of codeine sulfate and the following inactive ingredients: colloidal silicon dioxide, microcrystalline cellulose, pregelatinized starch, and stearic acid.

12 CLINICAL PHARMACOLOGY

12.1 Mechanism of Action

Codeine sulfate is an opioid analgesic, related to morphine, but with less potent analgesic properties. Codeine is selective for the mu receptor, but with a much weaker affinity than morphine. The analgesic properties of codeine have been speculated to come from its conversion to morphine, although the exact mechanism of analgesic action remains unknown.

Effects of the Central Nervous System (CNS)

The principal therapeutic action of codeine sulfate is analgesia. Although the precise mechanism of the analgesic action is unknown, specific CNS opiate receptors and endogenous compounds with morphine-like activity have been identified throughout the brain and spinal cord and are likely to play a role in the expression and perception of analgesic effects. Some other CNS effects of codeine include anxiolysis, euphoria, and feelings of relaxation. Codeine sulfate causes respiratory depression, in part by a direct effect on the brainstem respiratory centers. Codeine sulfate and other related opioids depress the cough reflex by direct effect on the cough center in the medulla. Codeine sulfate may also cause miosis.

Effects on the Gastrointestinal Tract and on Other Smooth Muscle

Gastric, biliary and pancreatic secretions may be decreased by codeine. Codeine also causes a reduction in motility and is associated with an increase in tone in the antrum of the stomach and duodenum. Digestion of food in the small intestine is delayed and propulsive contractions are decreased. Propulsive peristaltic waves in the colon are decreased, while tone is increased to the point of spasm. The end result may be constipation. Codeine can cause a marked increase in biliary tract pressure as a result of the spasm of the sphincter of Oddi. Codeine may also cause spasms of the sphincter of the urinary bladder.

Effects on the Cardiovascular System

Codeine produces peripheral vasodilation which may result in orthostatic hypotension and fainting. Release of histamine can occur, which may play a role in opioid-induced hypotension. Manifestations of histamine release and/or peripheral vasodilation may include pruritus, flushing, red eyes, and sweating.

Endocrine System

Opioid agonists such as codeine sulfate have been shown to have a variety of effects on the secretion of hormones. Opioids inhibit the secretion of ACTH, cortisol, and luteinizing hormone (LH) in humans. They also stimulate prolactin, growth hormone (GH) secretion, and pancreatic secretion of insulin and glucagons in humans and other species, rats and dogs. Thyroid stimulating hormone (TSH) has been shown to be both inhibited and stimulated by opioids.

Immune System

Codeine has been shown to have a variety of effects on components of the immune system in in vitro and animal models. The clinical significance of these findings is unknown.

12.2 Pharmacodynamics

Codeine concentrations do not correlate with brain concentration or relief of pain.

The minimum effective concentration varies widely and is influenced by a variety of factors, including the extent of previous opioid use, age and general medical condition. Effective doses in tolerant patients may be significantly higher than in opioid-naïve patients.

12.3 Pharmacokinetics Absorption

Codeine is absorbed from the gastrointestinal tract with maximum plasma concentration occurring 60 minutes post administration.

Food Effects

When 60 mg codeine sulfate was administered 30 minutes after ingesting a high fat/high calorie meal, there was no significant change in the rate and extent of absorption of codeine.

Steady-state

Administration of 15 mg codeine sulfate every four hours for 5 days resulted in steady-state concentrations of codeine, morphine, morphine-3-glucuronide (M3G) and morphine-6-glucuronide (M6G) within 48 hours.

Distribution

Codeine has been reported to have an apparent volume of distribution of approximately 3-6 L/kg, indicating extensive distribution of the drug into tissues. Codeine has low plasma protein binding with about 7-25% of codeine bound to plasma proteins.

Metabolism

About 70-80% of the administered dose of codeine is metabolized by conjugation with glucuronic acid to codeine-6-glucuronide (C6G) and via O-demethylation to morphine (about 5-10%) and N-demethylation to norcodeine (about 10%) respectively. UDP-glucuronosyltransferase (UGT) 2B7 and 2B4 are the major enzymes mediating glucurodination of codeine to C6G. Cytochrome P450 2D6 is the major enzyme responsible for conversion of codeine to morphine and P450 3A4 is the major enzyme mediating conversion of codeine to norcodeine. Morphine and norcodeine are further metabolized by conjugation with glucuronic acid. The glucuronide metabolites of morphine are morphine-3-glucuronide (M3G) and morphine-6-glucuronide (M6G). Morphine and M6G are known to have analgesic activity in humans. The analgesic activity of C6G in humans is unknown. Norcodeine and M3G are generally not considered to possess analgesic properties.

Elimination

Approximately 90% of the total dose of codeine is excreted through the kidneys, of which approximately 10% is unchanged codeine. Plasma half-lives of codeine and its metabolites have been reported to be approximately 3 hours.

13 NONCLINICAL TOXICOLOGY

13.1 Carcinogenesis, Mutagenesis, Impairment of Fertility

Carcinogenesis: Two year carcinogenicity studies have been conducted in F344/N rats and B6C3F1 mice. There was no evidence of carcinogenicity in male and female rats, respectively, at dietary doses up to 70 and 80 mg/kg/day of codeine (approximately 2 times the maximum recommended daily dose of 360 mg/day for adults on a mg/m^2 basis) for two years. Similiarly there was no evidence of carcinogenicity activity in male and female mice at dietary doses up to 400 mg/kg/day of codeine (approximately 5 times the maximum recommended daily dose of 360 mg/day for adults on a mg/m^2 basis) for two years.

Mutagenesis: Codeine was not mutatgenic in the in vitro bacterial reverse mutation assay or clastogenic in the in vitro Chinese hamster ovary cell chromosome aberration assay.

Impairment of fertility: No animal studies were conducted to evaluate the effect of codeine on male or female fertility.

13.3 Reproduction and Developmental Toxicology

Studies on the reproductive and developmental effects of codeine have been reported in the published literature in hamsters, rats, mice and rabbits.

A study in hamsters administered 150 mg/kg bid of codeine (PO; approximately 7 times the maximum recommended daily dose of 360 mg/day for adults on a mg/m^2 basis) reported the development of cranial malformations (i.e., meningoencephalocele) in several fetuses examined; as well as the observation of increases in the percentage of resorptions per litter examined. Doses of 50 and 150 mg/kg, bid resulted in fetotoxicity as demonstrated by decreased fetal body weight. In an earlier study in hamsters, doses of 73-360 mg/kg level (PO; approximately 2-8 times the maximum recommended daily dose of 360 mg/day for adults on a mg/m^2 basis), reportedly produced cranioschisis in all of the fetuses examined.

In studies in rats, doses at the 120 mg/kg level (PO; approximately 3 times the maximum recommended daily dose of 360 mg/day for adults on a mg/m^2 basis), in the toxic range for the adult animal, were associated with an increase in embryo resorption at the time of implantation.

In pregnant mice, a single 100 mg/kg dose (SC; approximately 1.4 times the recommended daily dose of 360 mg/day for adults on a mg/mg^2 basis) reportedly resulted in delayed ossification in the offspring.

No teratogenic effects were observed in rabbits administered up to 30 mg/kg (approximately 2 times the maximum recommended daily dose of 360 mg/day for adults on a mg/m^2 basis) of codeine during organogenesis.

16 HOW SUPPLIED/STORAGE AND HANDLING

Codeine Sulfate

60 mg Tablet: white, biconvex tablets scored on one side, with strength-indicating number “60” debossed on the scored side and product identification number “54 412” debossed on the other side.

NDC 54868-2541-0: Bottles of 10 Tablets

NDC 54868-2541-1: Bottles of 30 Tablets

NDC 54868-2541-2: Bottles of 60 Tablets

Storage

Store at Controlled Room Temperature, 15º to 30ºC (59º to 86ºF).

Protect from moisture and light.

Dispense in well-closed container as defined in the USP/NF.

All opioids are liable to diversion and misuse both by the general public and healthcare workers and should be handled accordingly.

17 PATIENT COUNSELING INFORMATION

- Advise patients that codeine sulfate is a narcotic pain reliever and may be habit forming. It should be taken only as directed.
- The dose of codeine sulfate should not be adjusted without consulting with your physician.
- Advise patients that codeine may cause drowsiness, dizziness, or lightheadedness and may impair the mental and/or physical abilities required for the performance of potentially hazardous tasks such as driving a car or operating machinery.
- Patients started on codeine sulfate or patients whose dose has been adjusted should refrain from any potentially dangerous activity until it is established that they are not adversely affected. Advise patients not to combine codeine sulfate with alcohol or other central nervous system depressants (sleep aids, tranquilizers) except by the orders of the prescribing physician, because dangerous additive effects may occur, resulting in serious injury or death.
- Advise patients that codeine sulfate is a potential drug of abuse, and should be protected from theft. It should never be given to anyone other than the individual for whom it was prescribed.
- Advise patients to keep codeine sulfate in a secure place out of the reach of children. When codeine sulfate is no longer needed the unused tablets should be destroyed by flushing down the toilet.
- Advise patients of the potential for severe constipation when taking codeine sulfate; appropriate laxatives and/or stool softeners as well as other appropriate treatments should be initiated from the onset of therapy.
- Advise patients of the most common adverse events that may occur while taking codeine sulfate: drowsiness, lightheadedness, dizziness, sedation, shortness of breath, nausea, vomiting, constipation, and sweating.
- Advise patients that some people have a genetic variation that results in their liver changing codeine into morphine more rapidly and completely than other people. These people are more likely to have higher-than-normal levels of morphine in their blood after taking codeine, which can result in overdose symptoms such as extreme sleepiness, confusion, or shallow breathing. In most cases, it is unknown if someone is an ultra-rapid codeine metabolizer. Nursing mothers taking codeine can also have higher morphine levels in their breast milk if they are ultra-rapid metabolizers. These higher levels of morphine in breast milk may lead to life-threatening or fatal side effects in nursing babies. Nursing mothers should be advised to watch for signs of morphine toxicity in their infants which includes increased sleepiness (more than usual), difficulty breastfeeding, breathing difficulties, or limpness. Instruct nursing mothers to talk to the baby’s doctor immediately if they notice these signs and, if they cannot reach the doctor right away, to take the baby to an emergency room or call 911 (or local emergency services).
- If patients have been receiving treatment with codeine sulfate for more than a few weeks and cessation of therapy is indicated, they should be counseled on the importance of safely tapering the dose and that abruptly discontinuing the medication could precipitate withdrawal symptoms. The physician should provide a dose schedule to accomplish a gradual discontinuation of the medication.
- Women of childbearing potential who become or are planning to become pregnant should consult a physician prior to initiating or continuing therapy with codeine sulfate.
- Safe use in pregnancy has not been established. Prolonged use of opioid analgesics during pregnancy may cause fetal/neonatal physical dependence, and neonatal withdrawal may occur.
  10005657/01 Revised July 2009
  © RLI, 2009

PACKAGE LABEL

NDC 54868-2541-0: Bottles of 10 Tablets, 60 mg

NDC 54868-2541-1: Bottles of 30 Tablets, 60 mg

NDC 54868-2541-2: Bottles of 60 Tablets, 60 mg